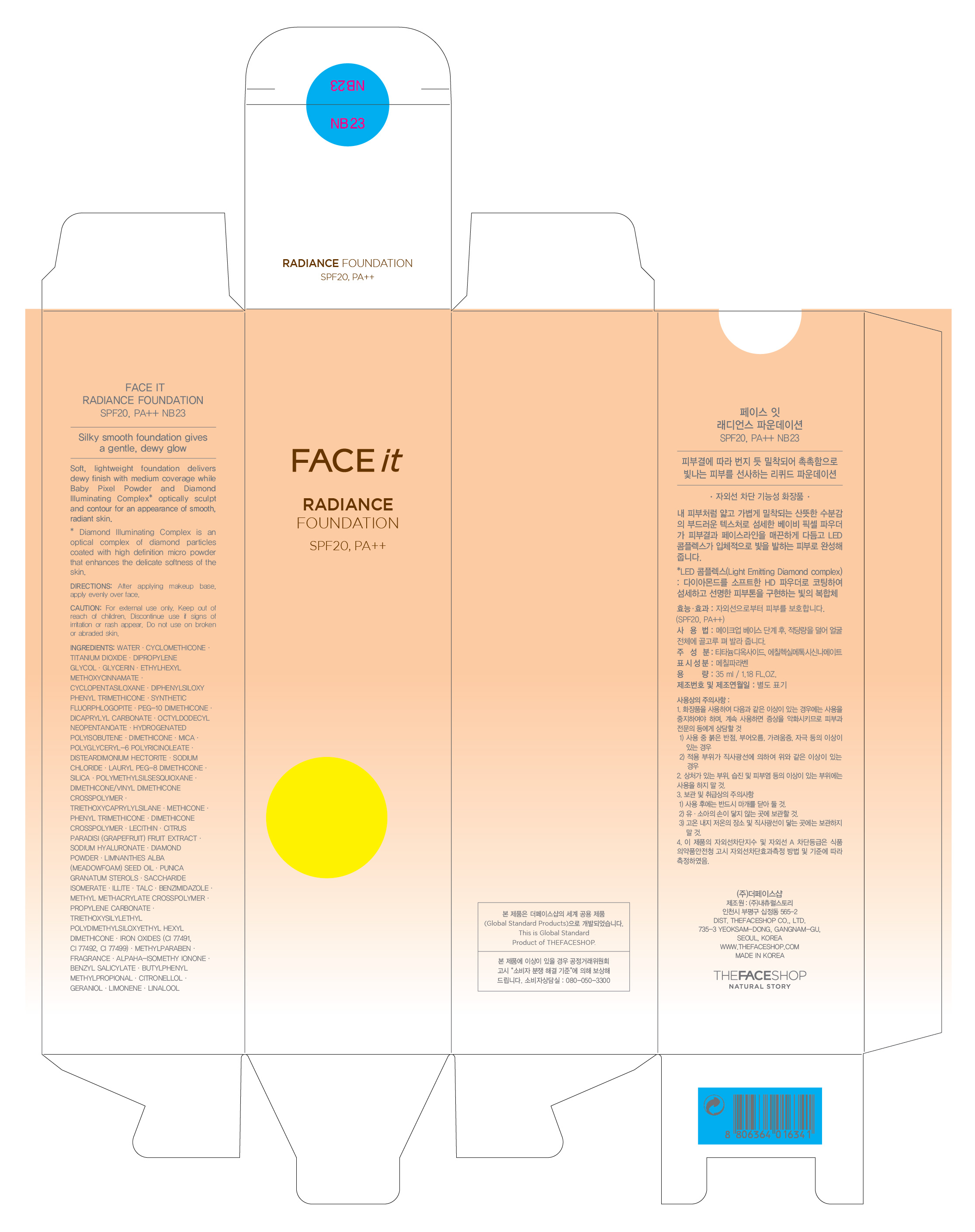 DRUG LABEL: FACE IT RADIANCE FOUNDATION SPF20 NB23
NDC: 51523-119 | Form: CREAM
Manufacturer: THEFACESHOP CO., LTD
Category: otc | Type: HUMAN OTC DRUG LABEL
Date: 20110913

ACTIVE INGREDIENTS: TITANIUM DIOXIDE 11.476 mL/100 mL; OCTINOXATE 4.5 mL/100 mL
INACTIVE INGREDIENTS: WATER; TRIETHOXYCAPRYLYLSILANE; TALC; MICA; SILICON DIOXIDE; CYCLOMETHICONE; DIPROPYLENE GLYCOL; GLYCERIN; DIMETHICONE; SODIUM CHLORIDE; DICAPRYLYL CARBONATE; OCTYLDODECYL NEOPENTANOATE; CYCLOMETHICONE 5; PHENYL TRIMETHICONE; PROPYLENE CARBONATE; GRAPEFRUIT; MEADOWFOAM SEED OIL; SACCHARIDE ISOMERATE; HYALURONATE SODIUM; DIAMOND TURBOT; BENZIMIDAZOLE; METHYLPARABEN; FERRIC OXIDE RED; FERRIC OXIDE YELLOW; FERROSOFERRIC OXIDE; ISOMETHYL-.ALPHA.-IONONE; BENZYL SALICYLATE; BUTYLPHENYL METHYLPROPIONAL; .BETA.-CITRONELLOL, (R)-; GERANIOL; LINALOOL, (+/-)-

FACE IT RADIANCE FOUNDATION SPF20 NB23

ACTIVE INGREDIENT

OCTINOXATE (4.5%)
TITANIUM DIOXIDE (11.476%)

INACTIVE INGREDIENT

CYCLOMETHICONE
SILICON DIOXIDE
MICA
MICA
TRIETHOXYCAPRYLYLSILANE
WATER
DIPROPYLENE GLYCOL
GLYCERIN
DIMETHICONE
SODIUM CHLORIDE
DICAPRYLYL CARBONATE
OCTYLDODECYL NEOPENTANOATE
CYCLOMETHICONE 5
PHENYL TRIMETHICONE
PROPYLENE CARBONATE
GRAPEFRUIT
MEADOWFOAM SEED OIL
SACCHARIDE ISOMERATE
HYALURONATE SODIUM
DIAMOND TURBOT
BENZIMIDAZOLE
METHYLPARABEN
FERRIC OXIDE RED
FERRIC OXIDE YELLOW
FERROSOFERRIC OXIDE
ISOMETHYL-.ALPHA.-IONONE
BENZYL SALICYLATE
BUTYLPHENYL METHYLPROPIONAL
.BETA.-CITRONELLOL, (R)-
GERANIOL
LINALOOL, (+/-)-

PURPOSE

Provides high protection against sunburn and tanning.

WHEN USING

Avoid contact with eyes.

STOP USE

Discontinue use if sign of irritation or rash appear.

DOSAGE AND ADMINISTRATION

Dispense an adequate amount and apply evenly. (At the final stage of basic skincare, dispense an adequate amount and apply evenly to desired parts)

PACKAGE LABEL

FACE IT RADIANCE FOUNDATION SPF20 NB23